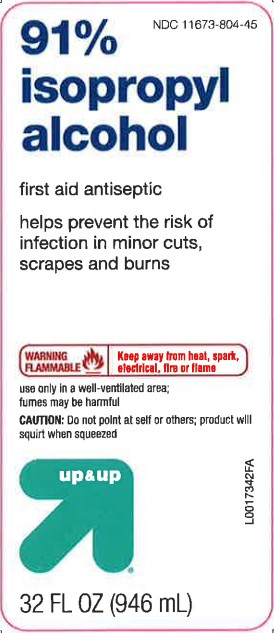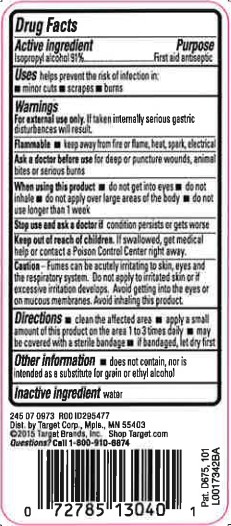 DRUG LABEL: Isopropyl Alcohol
NDC: 11673-804 | Form: LIQUID
Manufacturer: Target Corporation
Category: otc | Type: HUMAN OTC DRUG LABEL
Date: 20260218

ACTIVE INGREDIENTS: ISOPROPYL ALCOHOL 0.91 mg/1 mL
INACTIVE INGREDIENTS: WATER

Up & Up 804.003/804AA
91% Isopropyl Alcohol

Active Ingredient

Isopropyl alcohol 91%

Purpose

First aid antiseptic

Use

helps prevent the risk of infection in:

- minor cuts
- scrapes
- burns

Warnings

For external use only. If taken internally serious gastric disturbances will result.

Flammable

Keep away from fire or flame, heat, spark, electrical

Ask a doctor before use

if you have deep or puncture wounds, animal bites or serious burns

When using this product

- do not get into eyes
- do not inhale
- do not apply over large areas of the body
- do not use longer than 1 week

Stop use and ask a doctor if

- condition persists or gets worse

Keep out of reach of children.

If swallowed, get medical help or contact a Poison Control Center right away.

Caution

Fumes can be acutely irritating to skin, eyes and the respiratory system. Do not apply to irritated skin or if excessive irritation develops. Avoid getting into the eyes or on mucous membranes. Avoid inhaling this product.

Directions

- clean the affected area
- apply a small amount of this product on the area 1 to 3 times daily
- may be covered with a sterile bandage
- if bandaged, let dry first

other information

- does not contain, nor is intended as a substitute for grain or ethyl alcohol

Inactive ingredient

water

ADVERSE REACTION

Dist. by Target Corp. Mpls., MN 55403

©2015 Target Brands, Inc. Shop Target.com

Questions? Call 1-800-910-6874

Pat. D675, 101

principal display panel

NDC 11673-804-45

91% isopropyl alcohol

first aid antiseptic

helps prevent the risk of infection in minor cuts scrapes and burns

WARNING FLAMMABLE-Keep away from heat, spark, electrical, fire or flame

use only in a well-ventilated area; fumes may be harmful

CAUTION: Do not point at self or others; product will squirt when squeezed

up & up™

32 FL OZ (946 mL)